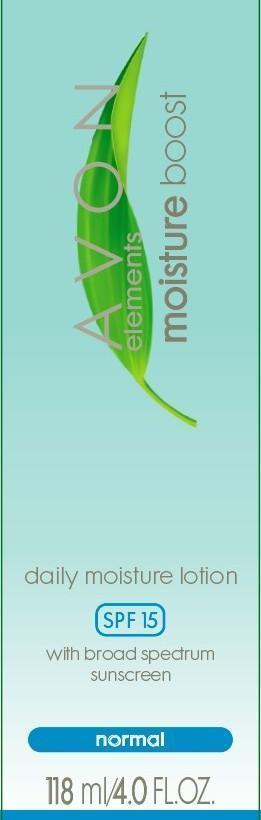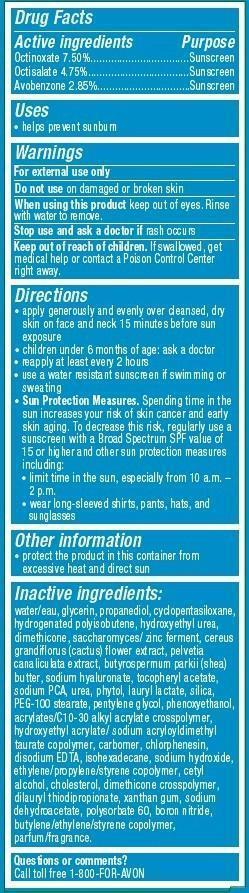 DRUG LABEL: Avon Elements
NDC: 10096-0301 | Form: LOTION
Manufacturer: New Avon LLC
Category: otc | Type: HUMAN OTC DRUG LABEL
Date: 20160219

ACTIVE INGREDIENTS: OCTINOXATE 75 mg/1 mL; OCTISALATE 47.5 mg/1 mL; AVOBENZONE 28.5 mg/1 mL

Active Ingredients
Octinoxate 7.50%....................................
Octisalate 4.75%.....................................
Avobenzone 2.85%.................................

Purpose
............... Sunscreen
............... Sunscreen
.............. Sunscreen

Uses

- helps prevent sunburn

Warnings
For external use only

Do not use on damaged or broken skin

When using this product keep out of eyes. Rinse with water to remove.

Stop use and ask a doctor if rash occurs

Keep out of reach of children. If swallowed, get medical help or contact a Poison Control Center right away.

Directions

- apply generously and evenly over cleansed, dry skin on face and neck 15 minutes before sun exposure
- children under 6 month of age:ask a doctor
- reapply at least every 2 hours
- use a water resistant sunscreen if swimming or sweating
- Sun Protection Measures. Spending time in the sun increases your risk of skin cancer and early skin aging. To decrease this risk, regularly use a sunscreen with a Broad Spectrum SPF value of 15 or higher and other sun protection measures including:
  • limit time in the sun, especially from 10 a.m. – 2 p.m.
  • wear long-sleeved shirts, pants, hats, and sunglasses

Other Information

- protect the product in this container from excessive heat and direct sun.

Inactive ingredients:
water/eau, glycerin, propanediol, cyclopentasiloxane, hydrogenated polyisobutene, hydroxyethyl urea, dimethicone, saccharomyces/ zinc ferment, cereus grandiflorus (cactus) flower extract, pelvetia canaliculata extract, butyrospermum parkii (shea) butter, sodium hyaluronate, tocopheryl acetate, sodium PCA, urea, phytol, lauryl lactate, silica, PEG-100 stearate, pentylene glycol, phenoxyethanol, acrylates/C10-30 alkyl acrylate crosspolymer, hydroxyethyl acrylate/ sodium acryloyldimethyl taurate copolymer, carbomer, chlorphenesin, disodium EDTA, isohexadecane, sodium hydroxide, ethylene/propylene/styrene copolymer, cetyl alcohol, cholesterol, dimethicone crosspolymer, dilauryl thiodipropionate, xanthan gum, sodium dehydroacetate, polysorbate 60, boron nitride, butylene/ethylene/styrene copolymer, parfum/fragrance.

Questions or comments?
Call toll free 1-800-FOR-AVON